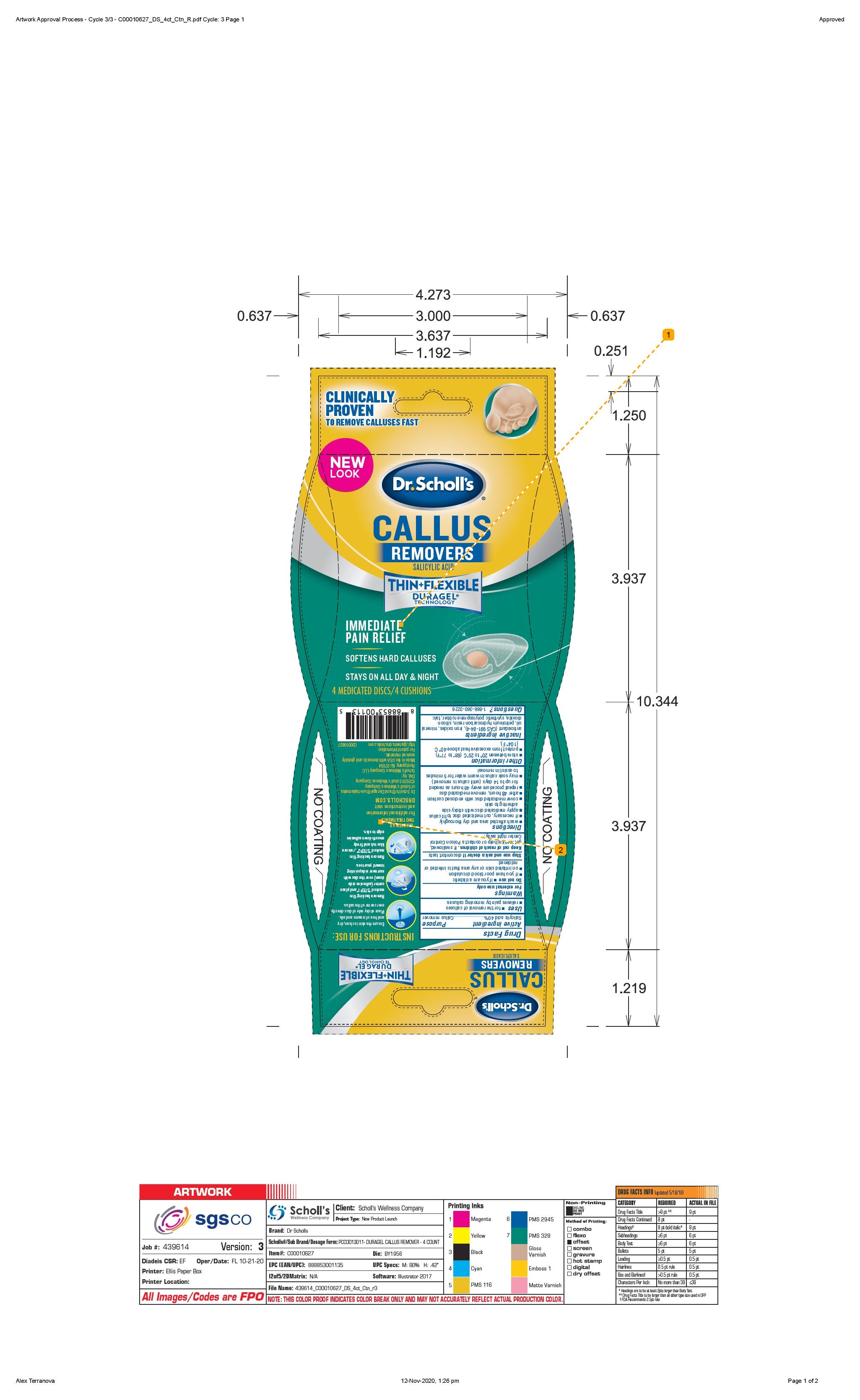 DRUG LABEL: Scholls Wellness Company LLC
NDC: 73469-0644 | Form: DISC
Manufacturer: Scholls Wellness Company LLC
Category: otc | Type: HUMAN OTC DRUG LABEL
Date: 20251221

ACTIVE INGREDIENTS: SALICYLIC ACID 0.4 g/1 g
INACTIVE INGREDIENTS: ANTIOXIDANT GS; BROWN IRON OXIDE; MINERAL OIL; SILICON DIOXIDE; TALC

(9000075) Duragel Callus Remover

Drug Facts

Active Ingredient

Active Ingredient Purpose

Salicylic Acid 40%........ Callus remover

Purpose

Callus remover

Uses

for the removal of calluses
relieves pain by removing calluses

Warnings

For external use only

Do not use

if you are a diabetic
if you have poor blood circulation
on irritated skin or any area that is infected or reddened

Stop use and ask a doctor if discomfort lasts

Keep out of reach of children. If swallowed,

get medical help or contact a Poison Control Center right away.

Directions

wash affected area and dry thoroughly

if necessary, cut medicated disc to fit callus

apply medicated disc with sticky side adhering to skin

cover medicated disc with enclosed cushion

after 48 hours, remove medicated disc

repeat procedure every 48 hours as needed for up to 14 days (until callus is removed)

may soak callus in warm water for 5 minutes to assist in removal

Other Information

store between 20ºC to 25ºC (68º to 77ºF).

Protect from excessive heat (temperatures above 40ºC (104ºF

Inactive Ingredients

Inactive ingredients antioxidant
(CAS 991-84-4), iron oxides, mineral oil,

petroleum hydrocarbon resin, silicon dioxide,

synthetic polyisoprene rubber, talc

Questions

Questions? 1-866-360-3226